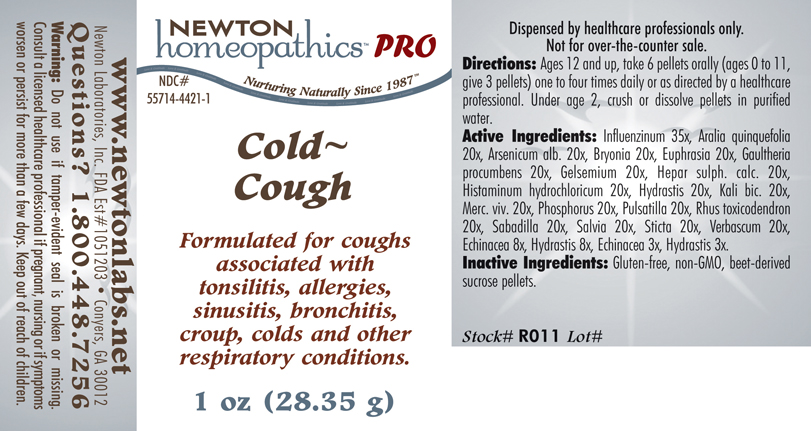 DRUG LABEL: Cold - Cough 
NDC: 55714-4421 | Form: PELLET
Manufacturer: Newton Laboratories, Inc.
Category: homeopathic | Type: HUMAN PRESCRIPTION DRUG LABEL
Date: 20110601

ACTIVE INGREDIENTS: Influenza A Virus 35 [hp_X]/1 g; American Ginseng 20 [hp_X]/1 g; Arsenic Trioxide 20 [hp_X]/1 g; Bryonia Alba Root 20 [hp_X]/1 g; Euphrasia Stricta 20 [hp_X]/1 g; Gaultheria Procumbens Top 20 [hp_X]/1 g; Gelsemium Sempervirens Root 20 [hp_X]/1 g; Calcium Sulfide 20 [hp_X]/1 g; Histamine Dihydrochloride 20 [hp_X]/1 g; Goldenseal 20 [hp_X]/1 g; Potassium Dichromate 20 [hp_X]/1 g; Mercury 20 [hp_X]/1 g; Phosphorus 20 [hp_X]/1 g; Pulsatilla Vulgaris 20 [hp_X]/1 g; Toxicodendron Pubescens Leaf 20 [hp_X]/1 g; Schoenocaulon Officinale Seed 20 [hp_X]/1 g; Sage 20 [hp_X]/1 g; Lobaria Pulmonaria 20 [hp_X]/1 g; Verbascum Thapsus 20 [hp_X]/1 g; Echinacea, Unspecified 8 [hp_X]/1 g; Influenza B Virus 35 [hp_X]/1 g
INACTIVE INGREDIENTS: Sucrose

Cold - Cough

INDICATIONS & USAGE SECTION

Cold Cough Formulated for coughs associated with tonsilitis, allergies, sinusitis, bronchitis, croup, colds and other respiratory conditions.

DOSAGE & ADMINISTRATION SECTION

Directions: Ages 12 and up, take 6 pellets orally (ages 0 to 11, give 3 pellets) one to four times daily or as directed by a healthcare professional. Under age 2, crush or dissolve pellets in purified water.

ACTIVE INGREDIENT SECTION

Influenzinum 35x, Aralia quinquefolia 20x, Arsenicum alb. 20x, Bryonia 20x, Euphrasia 20x, Gaultheria procumbens 20x, Gelsemium 20x, Hepar sulph. calc. 20x, Histaminum hydrochloricum 20x, Hydrastis 20x, Kali bic. 20x, Merc. viv. 20x, Phosphorus 20x, Pulsatilla 20x, Rhus toxicodendron 20x, Sabadilla 20x, Salvia 20x, Sticta 20x, Verbascum 20x, Echinacea 8x, Hydrastis 8x, Echinacea 3x, Hydrastis 3x.

PURPOSE SECTION

Formulated for coughs associated with tonsilitis, allergies, sinusitis, bronchitis, croup, colds and other respiratory conditions.

INACTIVE INGREDIENT SECTION

Inactive Ingredients: Gluten-free, non-GMO, beet-derived sucrose pellets.

QUESTIONS? SECTION

www.newtonlabs.net Newton Laboratories, Inc. FDA Est # 1051203 - Conyers, GA 30012
Questions? 1.800.448.7256

WARNINGS SECTION

Warning: Do not use if tamper- evident seal is broken or missing. Consult a licensed healthcare professional if pregnant, nursing or if symptoms worsen or persist for more than a few days. Keep out of reach of children.

PREGNANCY OR BREAST FEEDING SECTION

Consult a licensed healthcare professional if pregnant, nursing or if symptoms worsen or persist for more than a few days.

KEEP OUT OF REACH OF CHILDREN SECTION

Keep out of reach of children